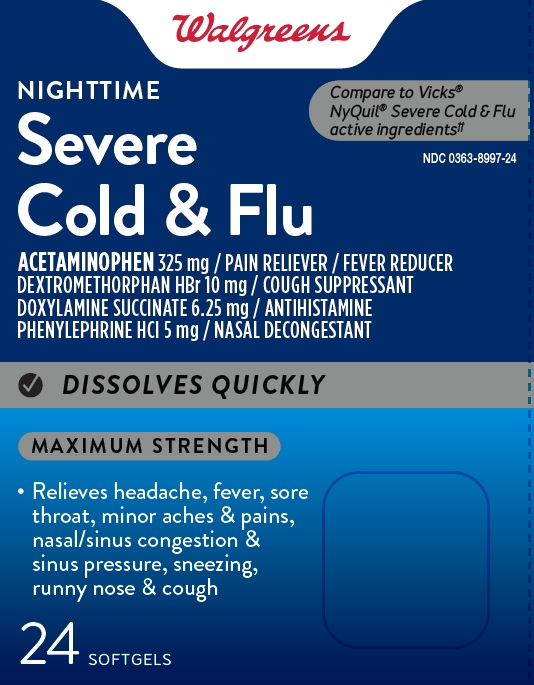 DRUG LABEL: SEVERE NIGHTTIME COLD AND FLU
NDC: 0363-8997 | Form: CAPSULE, GELATIN COATED
Manufacturer: WALGREENS
Category: otc | Type: HUMAN OTC DRUG LABEL
Date: 20260119

ACTIVE INGREDIENTS: ACETAMINOPHEN 325 mg/1 1; DEXTROMETHORPHAN HYDROBROMIDE 10 mg/1 1; DOXYLAMINE SUCCINATE 6.25 mg/1 1; PHENYLEPHRINE HYDROCHLORIDE 5 mg/1 1
INACTIVE INGREDIENTS: D&C YELLOW NO. 10; FD&C BLUE NO. 1; GELATIN; GLYCERIN; POLYETHYLENE GLYCOL 400; POVIDONE K30; PROPYLENE GLYCOL; WATER; SODIUM HYDROXIDE; SORBITOL; SORBITAN; TITANIUM DIOXIDE

SEVERE NIGHTTIME COLD AND FLU

Drug Facts

ACTIVE INGREDIENT

PURPOSE

Active ingredients (in each softgel) | Purposes
Acetaminophen 325 mg | Pain reliever/fever reducer
Dextromethorphan HBr 10 mg | Cough suppressant
Doxylamine succinate 6.25 mg | Antihistamine
Phenylephrine HCl 5 mg | Nasal decongestant

Uses

temporarily relieves common cold/flu symptoms:

- nasal congestion
- sinus congestion & pressure
- cough due to minor throat & bronchial irritation
- cough to help you sleep
- minor aches & pains
- headache
- fever
- sore throat
- runny nose & sneezing
- reduces swelling of nasal passages
- temporarily restores freer breathing through the nose
- promotes nasal and/or sinus drainage

Warnings

Liver warning

This product contains acetaminophen. Severe liver damage may occur if you take

- more than 4 doses in 24 hours, which is the maximum daily amount for this product
- with other drugs containing acetaminophen
- 3 or more alcoholic drinks every day while using this product

Sore throat warning

If sore throat is severe, persists for more than 2 days, is accompanied or followed by fever, headache, rash, nausea, or vomiting, consult a doctor promptly.

Allergy Alert

Acetaminophen may cause severe skin reactions. Symptoms may include:

- skin reddening
- blisters
- rash

If a skin reaction occurs, stop use and seek medical help right away.

Do not use

- with any other drug containing acetaminophen (prescription or nonprescription). If you are not sure whether a drug contains acetaminophen ask a doctor or pharmacist.
- if you are now taking a prescription monoamine oxidase inhibitor (MAOI) (certain drugs for depression, psychiatric or emotional conditions, or Parkinson's disease), or for 2 weeks after stopping the MAOI drug. If you do not know if your prescription drug contains an MAOI, ask a doctor or pharmacist before taking this product.
- to make a child sleep

Ask a doctor before use if you have

- liver disease
- heart disease
- high blood pressure
- thyroid disease
- diabetes
- glaucoma
- cough that occurs with too much phlegm (mucus)
- a breathing problem or chronic cough that lasts or as occurs with smoking, asthma, chronic bronchitis, or emphysema
- trouble urinating due to enlarged prostate gland

Ask a doctor or pharmacist before use if you are

- taking sedatives or tranquilizers
- taking the blood thinning drug warfarin

When using this product

- do not use more than directed
- excitability may occur, especially in children
- marked drowsiness may occur
- avoid alcoholic drinks
- be careful when driving a motor vehicle or operating machinery
- alcohol, sedatives, and tranquilizers may increase drowsiness

Stop use and ask a doctor if

- you get nervous, dizzy or sleepless
- pain, nasal congestion, or cough gets worse or lasts more than 7 days
- fever gets worse or lasts more than 3 days
- redness or swelling is present
- new symptoms occur
- cough comes back or occurs with rash or headache that lasts

These could be signs of a serious condition.

PREGNANCY OR BREAST FEEDING

If pregnant or breast-feeding, ask a health professional before use.

Keep out of reach of children.

Overdose warning

Taking more than directed can cause serious health problems. In case of overdose, get medical help or contact a Poison Control Center right away. Quick medical attention is critical for adults as well as for children even if you do not notice any signs or symptoms.

Directions

- take only as directed - see Overdose warning
- do not exceed 4 doses per 24 hours

adults & children 12 years & over | 2 softgels with water every 4 hours
children 4 to under 12 years | ask a doctor
children under 4 years | do not use

Other information

- store at room temperature

Inactive ingredients

D&C Yellow# 10, FD&C Blue# 1, gelatin, glycerin, polyethylene glycol, povidone, propylene glycol, purified water, sorbitol sorbitan, sodium hydroxide*, titanium dioxide
* may contain this ingredient

DISTRIBUTED BY: WALGREEN CO., 200 WILMOT RD., DEERFIELD, IL 60015

Questions or comments?

Call toll free: 1-888-333-9792

PRINCIPAL DISPLAY PANEL

Walgreens

Compare to Vicks® NyQuil® Severe

Cold & Flu active ingredients††

NIGHTTIME

Severe Cold & Flu

ACETAMINOPHEN/ PAIN RELIEVER/ FEVER REDUCER

DEXTROMETHORPHAN HBR/ COUGH SUPPRESSANT

DOXYLAMINE SUCCINATE/ ANTIHISTAMINE

PHENYLEPHRINE HCL/ NASAL DECONGESTANT

MAXIMUM STRENGTH

Relieves headache, fever, sore throat, minor
aches & pains, nasal/sinus congestion & sinus
pressure, sneezing, runny nose & cough

24

SOFTGELS